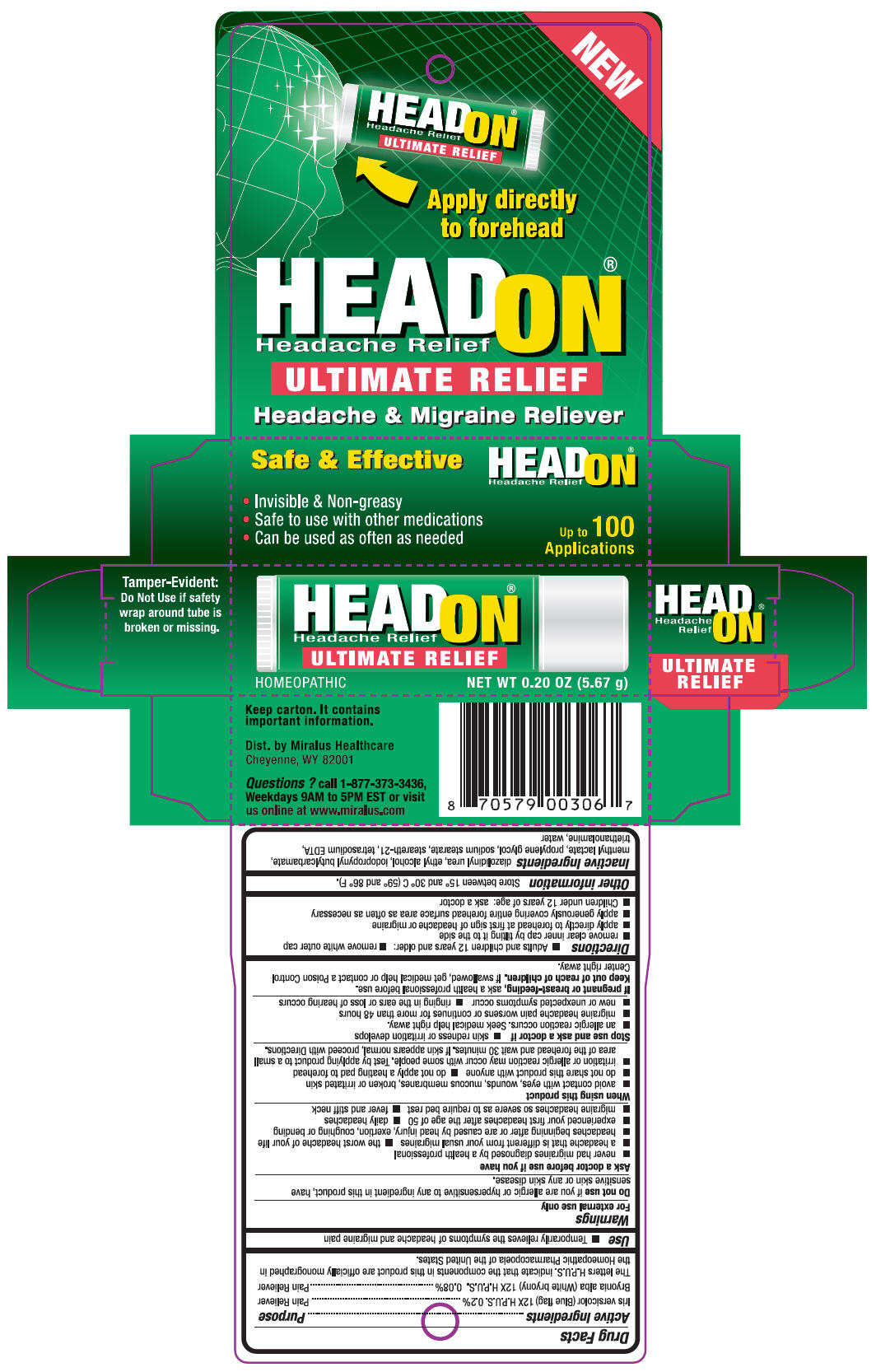 DRUG LABEL: HeadOn
NDC: 67567-0306 | Form: STICK
Manufacturer: American Health Distributions Inc.
Category: homeopathic | Type: HUMAN OTC DRUG LABEL
Date: 20100610

ACTIVE INGREDIENTS: Iris Versicolor Root 12 [hp_X]/1 1; Bryonia Alba Root 12 [hp_X]/1 1
INACTIVE INGREDIENTS: diazolidinyl urea; alcohol; iodopropynyl butylcarbamate; menthyl lactate; propylene glycol; sodium stearate; EDETATE sodium; trolamine; water

HEADON®

Drug Facts

ACTIVE INGREDIENT

Active Ingredients | Purpose
Iris versicolor (Blue flag) 12X H.P.U.S. 0.2% | Pain Reliever
Bryonia alba (White bryony) 12X H.P.U.S. 0.08% | Pain Reliever

The letters H.P.U.S. indicate that the components in this product are officially monographed in the Homeopathic Pharmacopoeia of the United States.

Use

- Temporarily relieves the symptoms of headache and migraine pain

Warnings

For external use only

Do not use if you are allergic or hypersensitive to any ingredient in this product, have sensitive skin or any skin disease.

Ask a doctor before use if you have

- never had migraines diagnosed by a health professional
- a headache that is different from your usual migraines
- the worst headache of your life
- headaches beginning after or are caused by head injury, exertion, coughing or bending
- experienced your first headaches after the age of 50
- daily headaches
- migraine headaches so severe as to require bed rest
- fever and stiff neck

When using this product

- avoid contact with eyes, wounds, mucous membranes, broken or irritated skin
- do not share this product with anyone
- do not apply a heating pad to forehead
- irritation or allergic reaction may occur with some people. Test by applying product to a small area of the forehead and wait 30 minutes. If skin appears normal, proceed with Directions.

Stop use and ask a doctor if

- skin redness or irritation develops
- an allergic reaction occurs. Seek medical help right away.
- migraine headache pain worsens or continues for more than 48 hours
- new or unexpected symptoms occur
- ringing in the ears or loss of hearing occurs

PREGNANCY OR BREAST FEEDING

If pregnant or breast-feeding, ask a health professional before use.

Keep out of reach of children. If swallowed, get medical help or contact a Poison Control Center right away.

Directions

- Adults and children 12 years and older:
- remove white outer cap
- remove clear inner cap by tilting it to the side
- apply directly to forehead at first sign of headache or migraine
- apply generously covering entire forehead surface area as often as necessary
- Children under 12 years of age: ask a doctor

Other information

Store between 15° and 30° C (59° and 86° F).

Inactive Ingredients

diazolidinyl urea, ethyl alcohol, iodopropynyl butylcarbamate, menthyl lactate, propylene glycol, sodium stearate, steareth-21, tetrasodium EDTA, triethanolamine, water

Dist. by Miralus Healthcare
Cheyenne, WY 82001

Questions ?

call 1-877-373-3436, Weekdays 9AM to 5PM EST or visit us online at www.miralus.com

PRINCIPAL DISPLAY PANEL - 5.67 gram canister carton

NEW

Apply directly
to forehead

HEADON®
Headache Relief

ULTIMATE RELIEF

Headache & Migraine Reliever